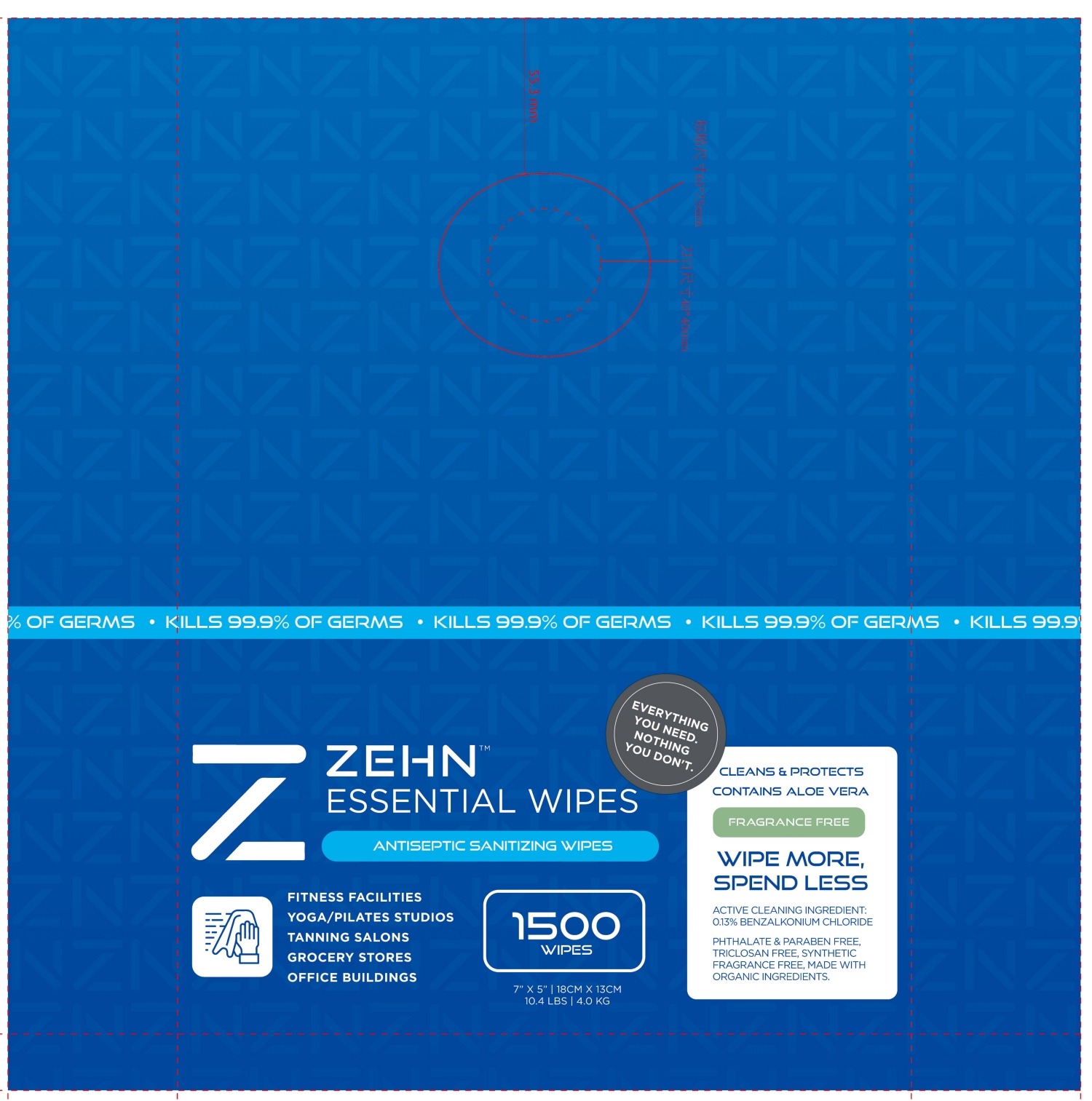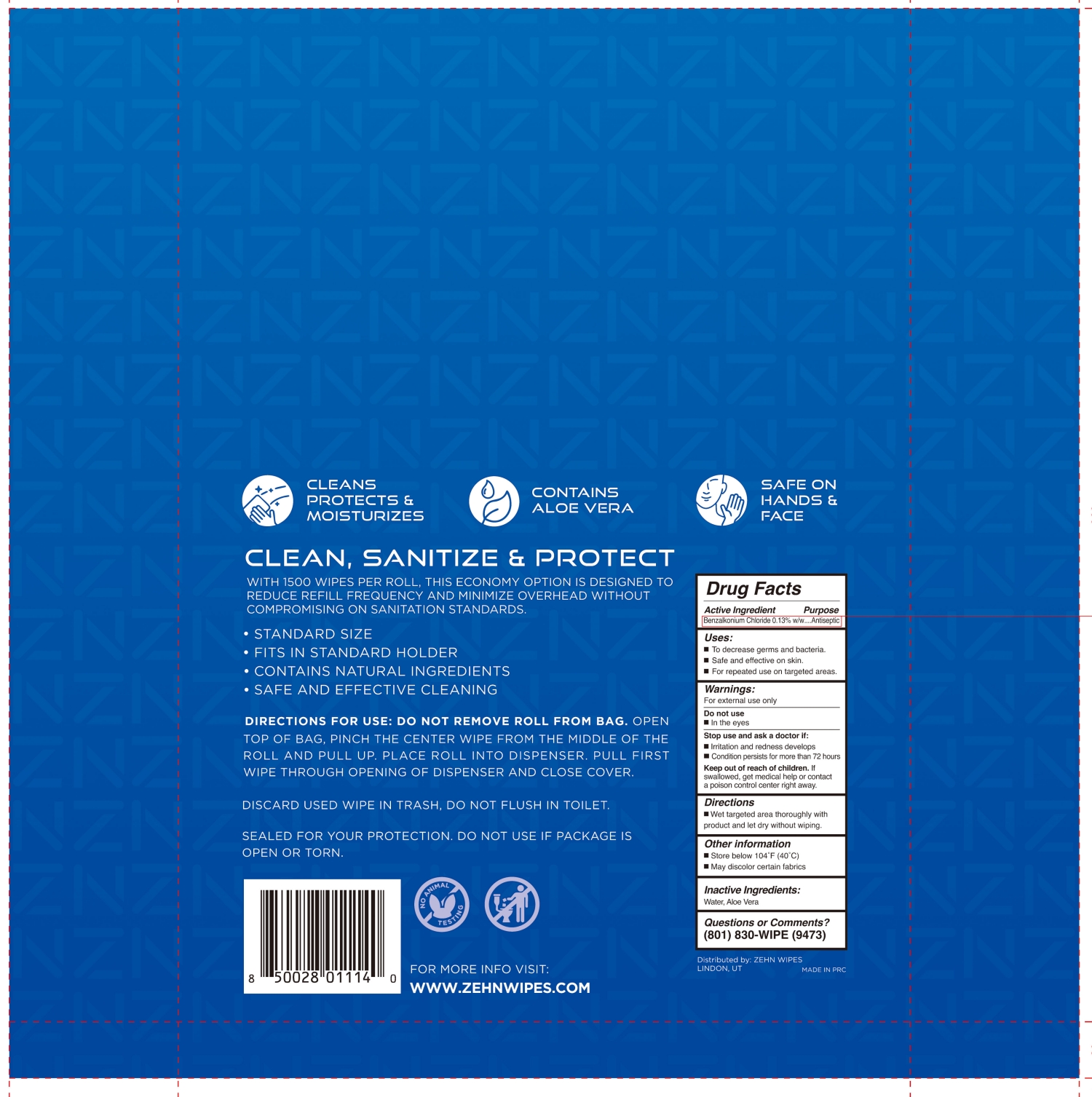 DRUG LABEL: ZEHN ANTISEPTIC SANITIZING WIPES
NDC: 84488-002 | Form: CLOTH
Manufacturer: Zehn Wipes
Category: otc | Type: HUMAN OTC DRUG LABEL
Date: 20251224

ACTIVE INGREDIENTS: BENZALKONIUM CHLORIDE 0.13 g/100 g
INACTIVE INGREDIENTS: ALOE VERA LEAF; WATER

84488-002 ZEHN ANTISEPTIC SANITIZING WIPES

Active Ingredient

Benzalkonium Chloride 0.13 % w/w

Purpose

Antiseptic

Uses:

■ To decrease germs and bacteria.

■ Safe and effective on skin.

■ For repeated use on targeted areas.

Warnings:

For external use only

Do not use

■ In the eyes

Stop use and ask a doctor if:

■ Irritation and redness develops

■ Condition persists for more than 72 hours

Keep out of reach of children. If

swallowed, get medical help or contact

a poison control center right away.

Directions

■ Wet targeted area thoroughly with

product and let dry without wiping.

Other information

■ Store below 104˚F (40˚C)

■ May discolor certain fabrics

Inactive Ingredients:

Water, Aloe Vera

PACKAGE LABEL

1500
WIPES
7'' × 5'' │18CM × 13CM
10.4 LBS│4.0 KG

NDC: 84488-002-01